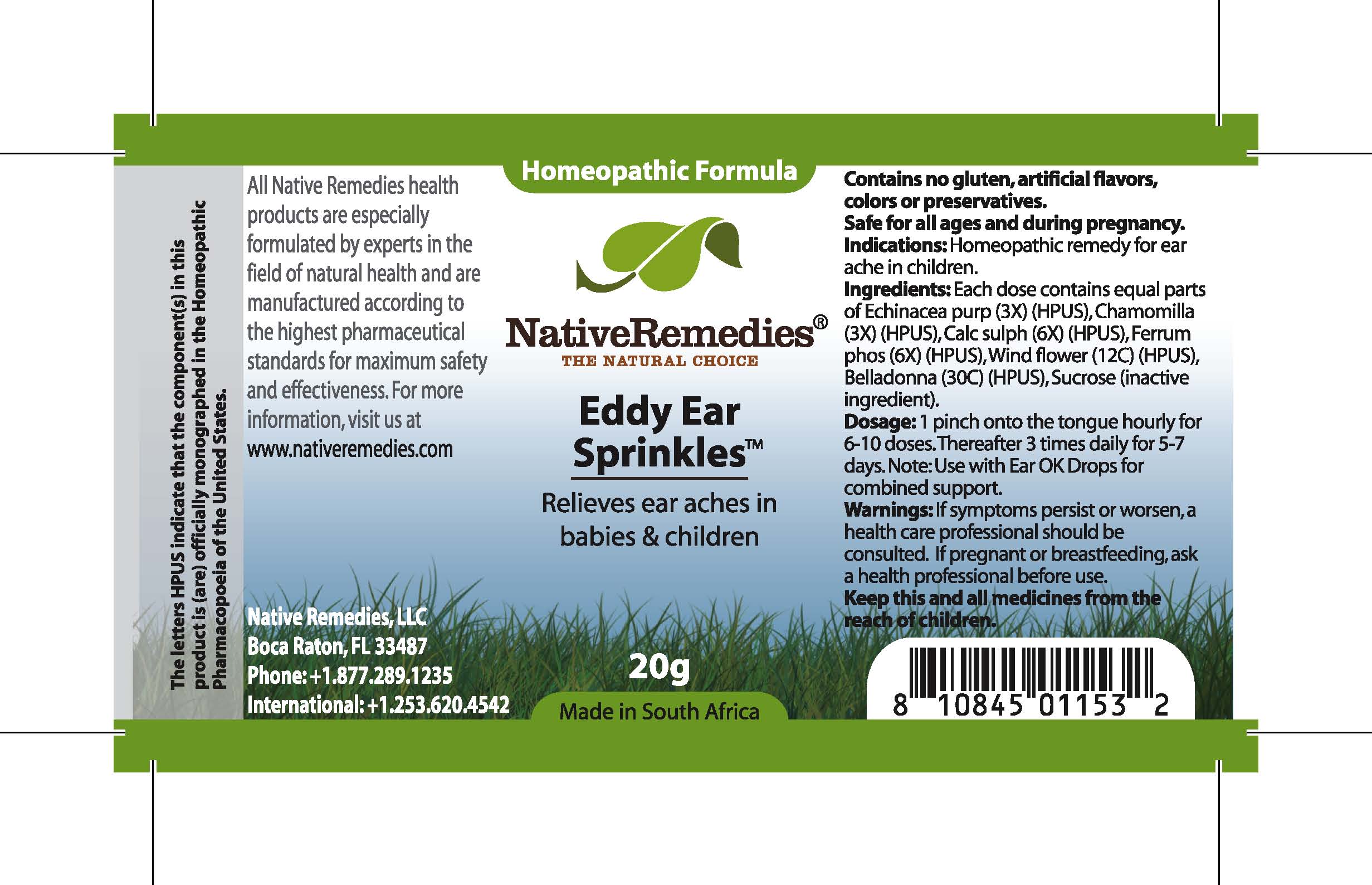 DRUG LABEL: Eddy Ear Sprinkles
NDC: 68647-161 | Form: GRANULE
Manufacturer: Feelgood Health
Category: homeopathic | Type: HUMAN OTC DRUG LABEL
Date: 20100722

ACTIVE INGREDIENTS: ECHINACEA PURPUREA 3 [hp_X]/33.3 mg; CHAMOMILE 3 [hp_X]/33.3 mg; CALCIUM SULFATE ANHYDROUS 6 [hp_X]/33.3 mg; FERRUM PHOSPHORICUM 6 [hp_X]/33.3 mg; PULSATILLA VULGARIS 12 [hp_C]/33.3 mg; ATROPA BELLADONNA 30 [hp_C]/33.3 mg
INACTIVE INGREDIENTS: SUCROSE 20000 mg/20000 mg

EDDY EAR SPRINKLES

PURPOSE

Relieves ear aches in babies and children

Indications: Homeopathic remedy for ear ache in children.

DOSAGE AND ADMINISTRATION

Dosage: 1 pinch onto the tongue hourly for 6-10 doses. Thereafter 3 times daily for 5-7 days. Use with Ear OK Drops™ for combined support.

GENERAL PRECAUTIONS

Caution: If symptoms persist or worsen, a health care professional should be consulted.

ACTIVE INGREDIENT

Ingredients: Each dose contains equal parts of Echinacea purp (3X) (HPUS), Chamomilla (3X) (HPUS), Calc sulph (6X) (HPUS), Ferrum phos (6X) (HPUS), Pulsatilla (12C) (HPUS), Belladonna (30C) (HPUS)

Sucrose (inactive ingredient).

PREGNANCY

If pregnant or breastfeeding, ask a health professional before use.

WARNINGS

Contains no gluten, artificial flavors, colors or preservatives. Safe for all ages and during pregnancy.

PATIENT COUNSELING INFORMATION

All Native Remedies health products are especially formulated by experts in the field of natural health and are manufactured according to the highest pharmaceutical standards for maximum safety and effectiveness. For more information, visit us at www.nativeremedies.com

Distributed by

Native Remedies, LLC

6531 Park of Commerce Blvd.

Suite 160

Boca Raton, FL 33487

Phone: 1.877.289.1235

International: + 1.561.999.8857

The letters HPUS indicate that the component(s) in this product is (are) officially monographed in the Homeopathic Pharmacopoeia of the United States.

KEEP OUT OF REACH OF CHILDREN

Keep this and all medicines from the reach of children.